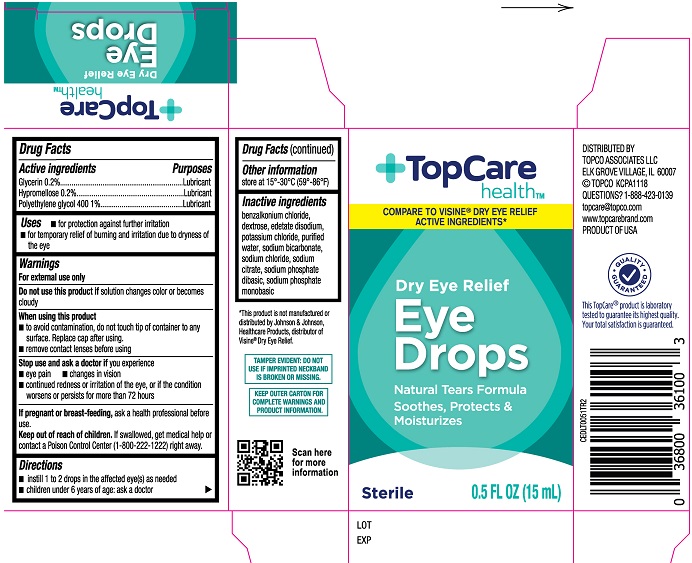 DRUG LABEL: TopCare Health Dry Eye Relief Eye Drops
NDC: 36800-845 | Form: SOLUTION
Manufacturer: Topco Associates LLC
Category: otc | Type: HUMAN OTC DRUG LABEL
Date: 20231220

ACTIVE INGREDIENTS: POLYETHYLENE GLYCOL 400 1 g/100 mL; HYPROMELLOSE, UNSPECIFIED 0.2 g/100 mL; GLYCERIN 0.2 g/100 mL
INACTIVE INGREDIENTS: BENZALKONIUM CHLORIDE; DEXTROSE; POTASSIUM CHLORIDE; WATER; SODIUM BICARBONATE; SODIUM CHLORIDE; SODIUM PHOSPHATE, MONOBASIC; EDETATE DISODIUM; SODIUM CITRATE; SODIUM PHOSPHATE, DIBASIC

Topcare Health Dry Eye (PLD)

Active ingredients

Glycerin ................... 0.2%

Hypromellose ........... 0.2%

Polyethylene glycol 400 ......1%

Purposes

Glycerin.......................Lubricant

Hypromellose..............Lubricant

Polyethylene glycol 400.........Lubricant

Uses

- for protection against further irritation
- for temporary relief of burning and irritation due to dryness of the eye

Warnings

For external use only

Do not use this product if solution changes color or becomes cloudy

When using this product

- to avoid contamination, do not touch tip of container to any surface. Replace cap after using.

Stop use and ask a doctor if you experience

- eye pain
- changes in vision
- continued redness or irritation of the eye, or if the condition worsens or persists for more than 72 hours

If pregnant or breast-feeding,

ask a health professional before use.

Keep out of reach of children.

If swallowed , get medical help or contact a Poison Control Center (1-800-222-1222), right away.

Directions

- instill 1 to 2 drops in the affected eye(s) as needed
- children under 6 years of age: ask a doctor

Other information

store at 15º-30ºC (59º-86ºF)

Inactive ingredients

benzalkonium chloride, dextrose, edetate disodium, potassium chloride, purified water, sodium bicarbonate, sodium chloride, sodium citrate, sodium phosphate dibasic, sodium phosphate monobasic